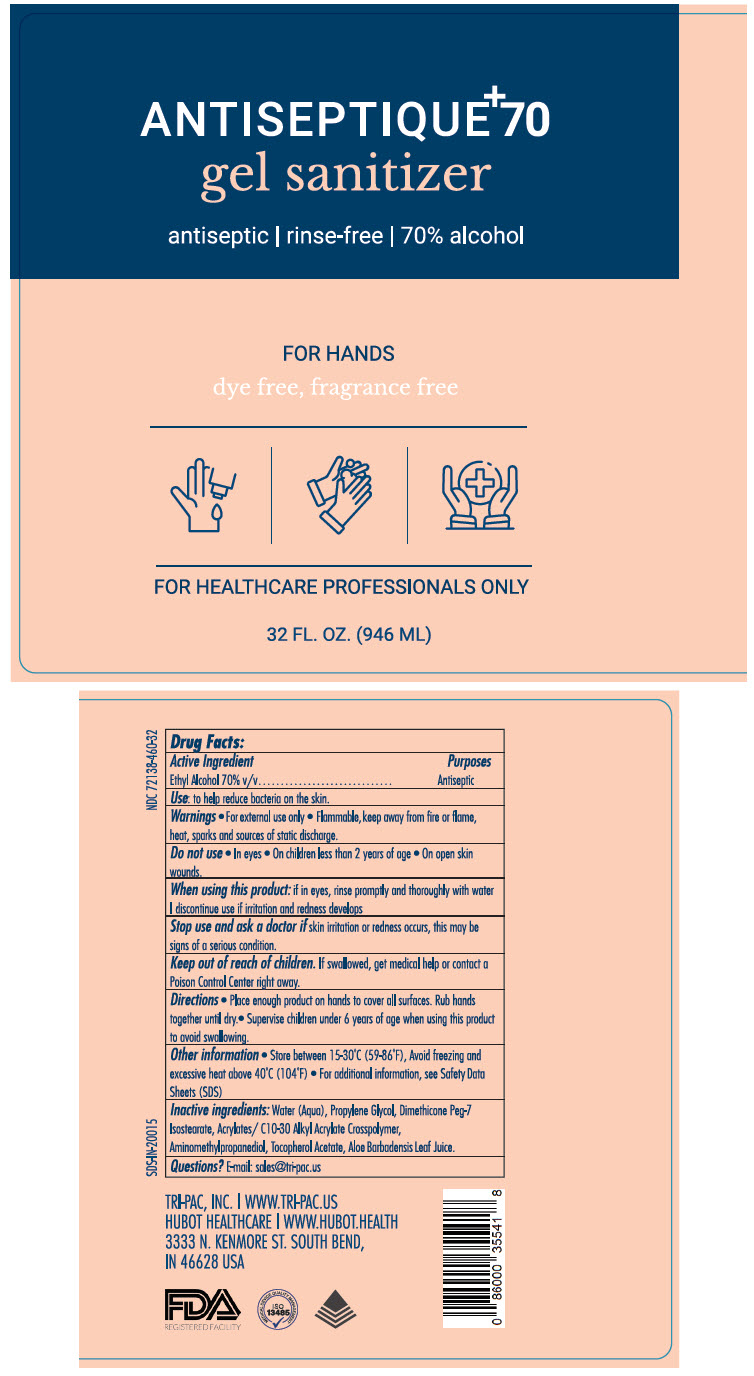 DRUG LABEL: Antiseptique 70
NDC: 72138-460 | Form: GEL
Manufacturer: Hubot Healthcare LLC
Category: otc | Type: HUMAN OTC DRUG LABEL
Date: 20200629

ACTIVE INGREDIENTS: ALCOHOL 70 mL/100 mL
INACTIVE INGREDIENTS: Water; Propylene Glycol; AMINOMETHYLPROPANOL; DIMETHICONE PEG-8 ISOSTEARATE; CARBOMER INTERPOLYMER TYPE A (ALLYL SUCROSE CROSSLINKED); Tocopherol; Aloe Vera Leaf

Antiseptique^+70

Drug Facts

Active ingredient

Ethyl Alcohol 70% v/v

Purposes

Antiseptic

Uses

to help reduce bacteria on skin

Warnings

|For external use only | Flammable, keep away from fire or flame, heat, sparks, and sources of static discharge

Do not use

|In eyes | On children less than 2 years of age | On open skin wounds

When using this product

|If in eyes, rinse promptly and thoroughly with water | Discontinue use if irritation and redness develops

Stop use and ask a doctor if skin irritation or redness occurs or persists for more than 72 hours.

Keep out of reach of children. If swallowed, get medical help or contact a Poison Control Center right away.

Directions

|Place enough product on hands to cover all surfaces. Rub hands together until dry | Supervise children under 6 years of age when using this product to avoid swallowing.

Other Information

| Store between 15-30C (59-86F). Avoid freezing and excessive heat above 40C (104F) | For additional information, see Safety Data Sheets (SDS)

Inactive Ingredients

water (aqua), propylene glycol, dimethicone PEG-7 Isostearate, acrylates/ C10-30 Alkyl Acrylate Crosspolymer, aminomethylpropanediol, tocopherol acetate, aloe barbadensis leaf juice

Questions?

sales@tri-pac.us

PRINCIPAL DISPLAY PANEL - 946 ML Bottle Label

ANTISEPTIQUE^+70
gel sanitizer

antiseptic | rinse-free | 70% alcohol

FOR HANDS
dye free, fragrance free

FOR HEALTHCARE PROFESSIONALS ONLY

32 FL. OZ. (946 ML)